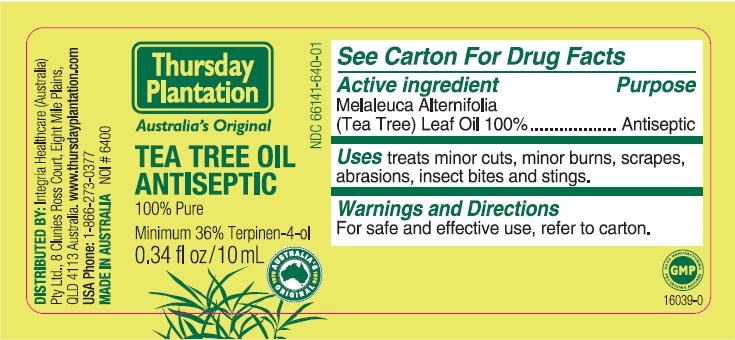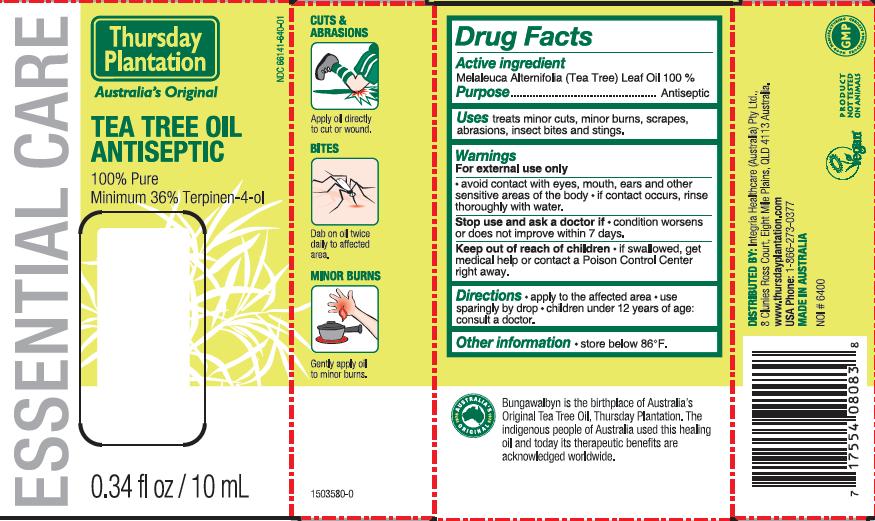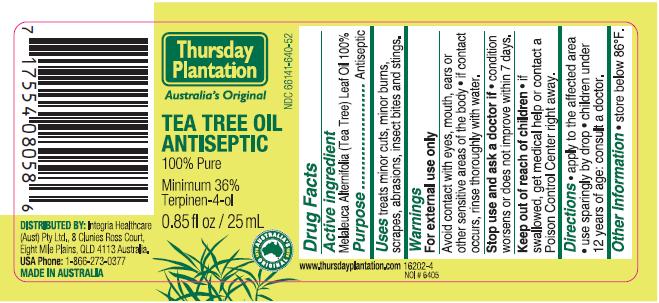 DRUG LABEL: Thursday Plantation
NDC: 66141-640 | Form: OIL
Manufacturer: Integria Healthcare Ballina
Category: otc | Type: HUMAN OTC DRUG LABEL
Date: 20100222

ACTIVE INGREDIENTS: TEA TREE OIL 25 mL/25 mL

ACTIVE INGREDIENT

Melaleuca Alternifolia (Tea Tree) Leaf Oil 100% ...... Antiseptic

INDICATIONS AND USAGE

Uses: treats minor cuts, minor burns, scrapes, abrasions, insect bites and stings.

WARNINGS

For external use only.

Avoid contact with eyes, mouth, ears or other sensitive areas of the body. If contact occurs, rinse thoroughly with water.

Stop use and ask a doctor if condition worsens or does not improve within 7 days.

Keep out of reach of children. If swallowed, get medical help or contact a Poison Control Center right away.

PURPOSE

Antiseptic

DOSAGE AND ADMINISTRATION

Directions: apply to the affected area. Use sparingly by drop. Children under 12 years of age: consult a doctor.

STORAGE AND HANDLING

store below 86 degrees F.

PACKAGE LABEL

Thursday Plantation

Australia's Original

Tea Tree Antiseptic

100% Pure

Minimum 36% Terpinen-4-ol

Distributed By:
Integria Healthcare Australia
Pty Ltd 8 Clunies Ross Court
Eight Mile Plains, QLD 4113
Australia
www.thursdayplantation.com
USA Phone: 1-866-273-0377
Made in Australia